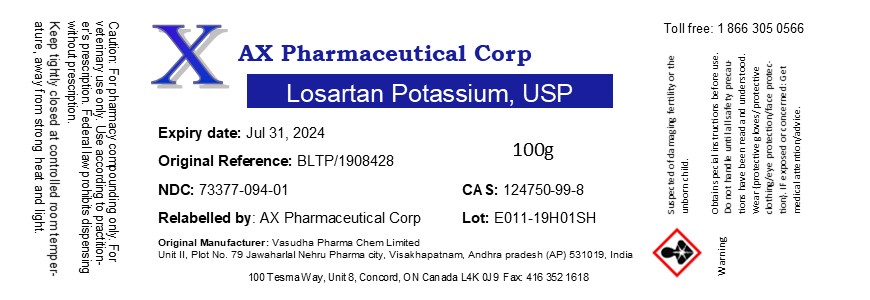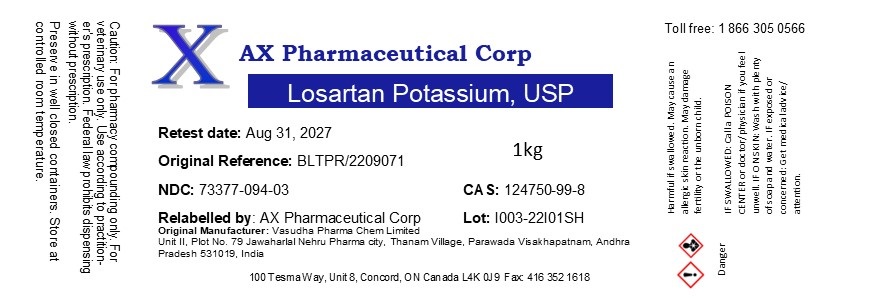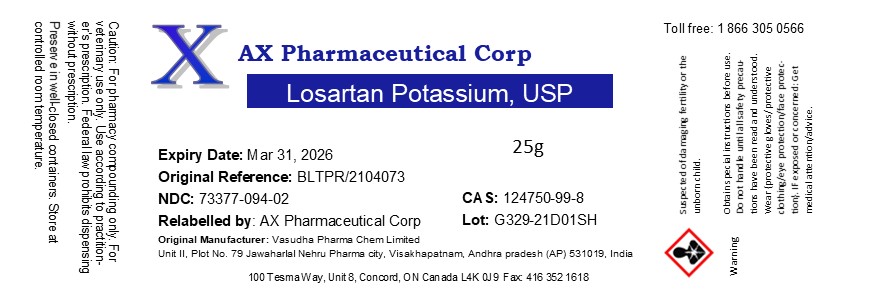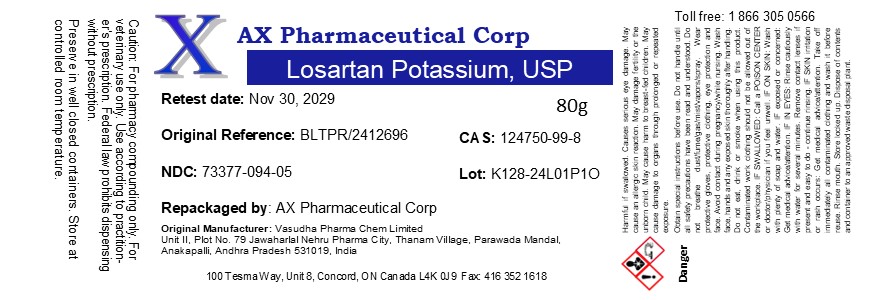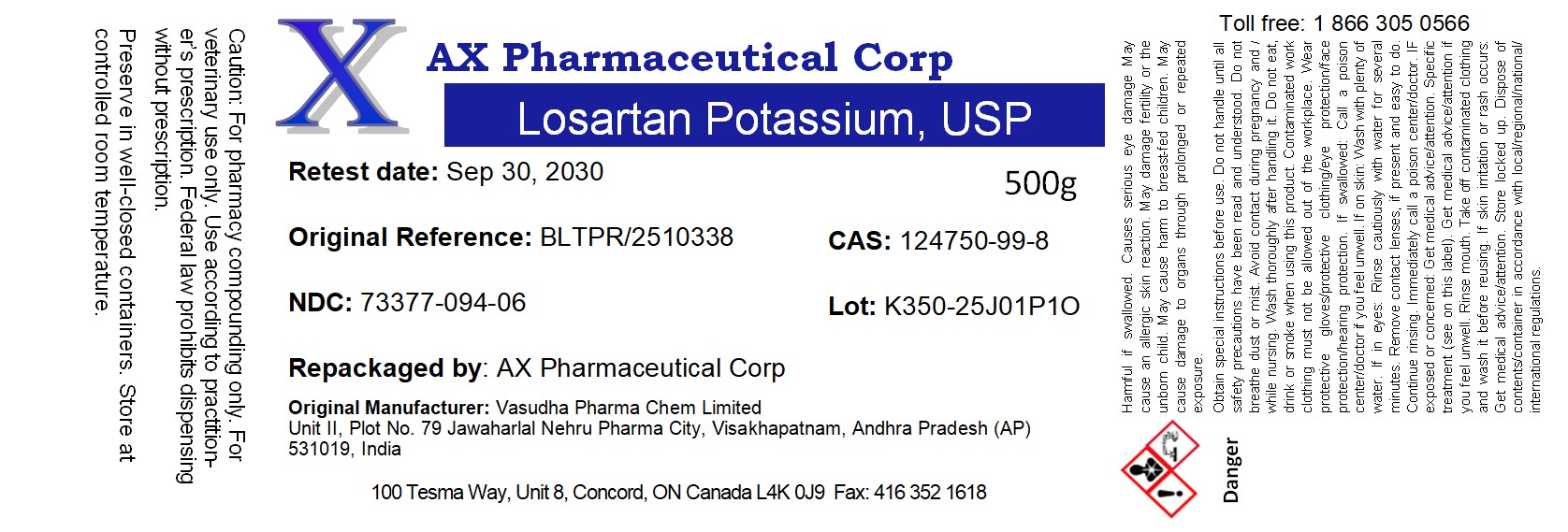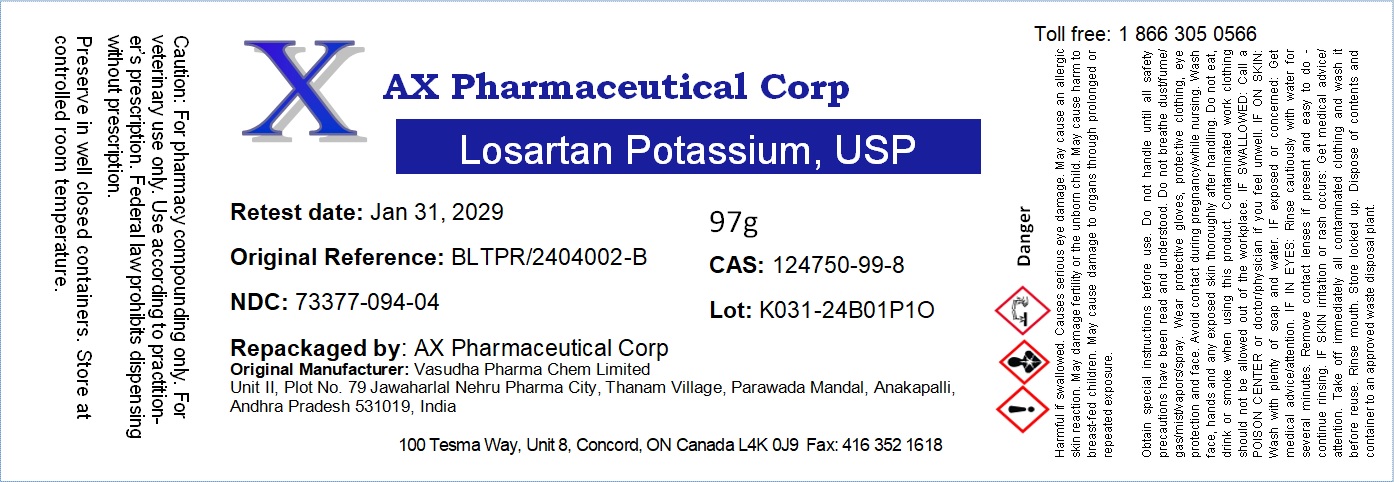 DRUG LABEL: Losartan Potassium
NDC: 73377-094 | Form: POWDER
Manufacturer: AX Pharmaceutical Corp
Category: other | Type: BULK INGREDIENT - ANIMAL DRUG
Date: 20260204

ACTIVE INGREDIENTS: LOSARTAN POTASSIUM 1 g/1 g

Losartan Potassium